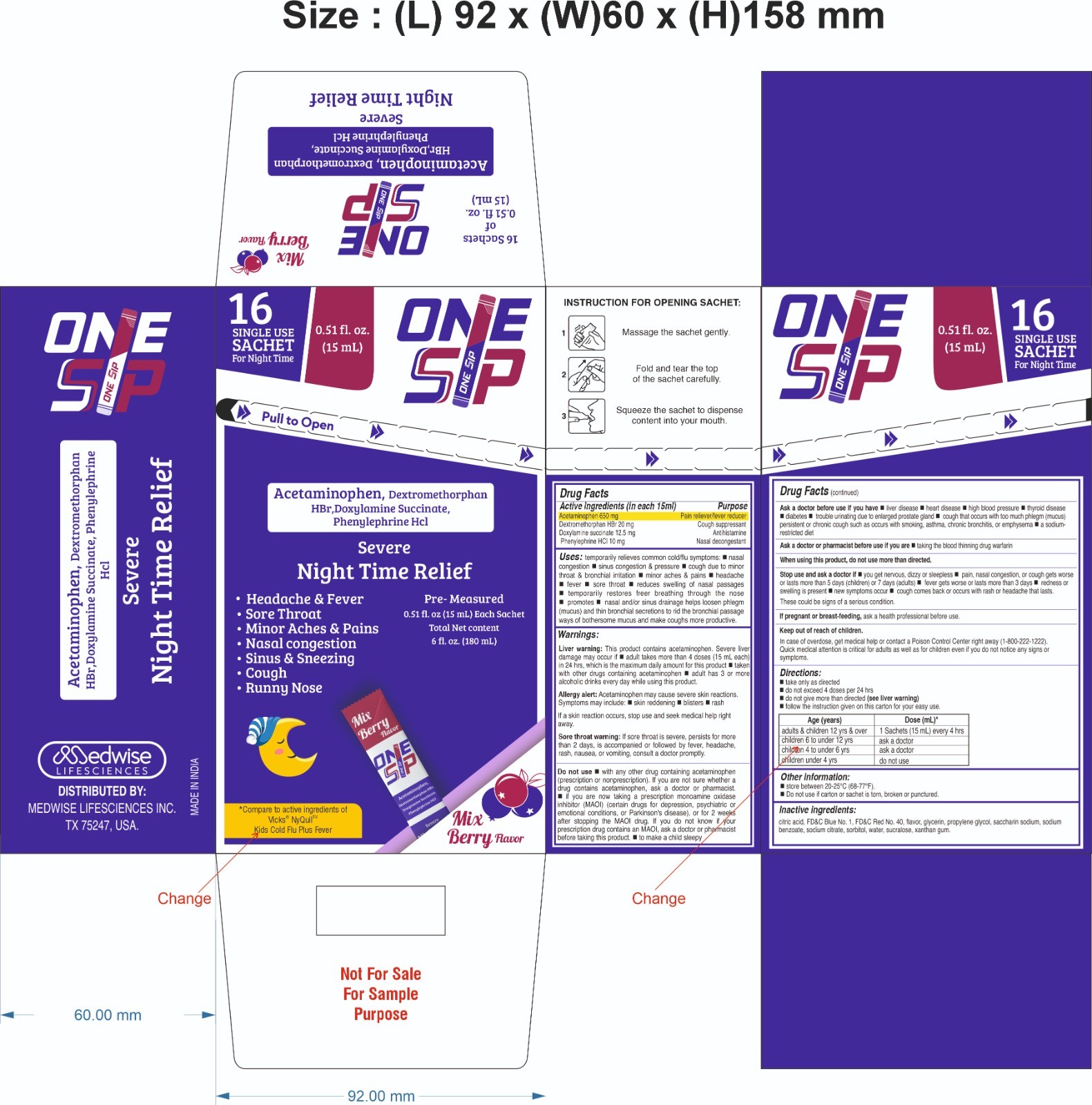 DRUG LABEL: ONESSIP ADULT NIGHTTIME SEVERE COLD AND FLU
NDC: 87078-872 | Form: SOLUTION
Manufacturer: MEDWISE LIFESCIENCES INC.
Category: otc | Type: HUMAN OTC DRUG LABEL
Date: 20260128

ACTIVE INGREDIENTS: PHENYLEPHRINE HYDROCHLORIDE 10 mg/15 mL; DEXTROMETHORPHAN HYDROBROMIDE 20 mg/15 mL; ACETAMINOPHEN 650 mg/15 mL; DOXYLAMINE SUCCINATE 12.5 mg/15 mL
INACTIVE INGREDIENTS: EDETATE DISODIUM; GLYCERIN; PROPYLENE GLYCOL; SORBITOL SOLUTION; MENTHOL, UNSPECIFIED FORM; ANHYDROUS CITRIC ACID; SODIUM SACCHARIN; SODIUM BENZOATE; XANTHAN GUM; FD&C RED NO. 40; WATER; SODIUM CITRATE; SUCRALOSE; STEVIA LEAF; FD&C BLUE NO. 2

OneSsip Night Time Adult Severe Cold & Flu 15 mL Sachet Drug Facts

Active ingredients (in each 15 mL)

Acetaminophen 650 mg

Dextromethorphan HBr 20 mg

Doxylamine Succinate 12.5 mg

Phenylephrine HCl 10 mg

Purpose
Pain reliever/fever reducer
Cough suppressant
Antihistamine
Nasal decongestant

Uses

- temporarily relieves common cold/flu symptoms:
  - nasal congestion
  - sinus congestion & pressure
  - cough due to minor throat & bronchial irritation
  - minor aches & pains
  - headache
  - fever
  - sore throat
  - runny nose & sneezing
  - reduces swelling of nasal passages
  - temporarily restores freer breathing through the nose
  - promotes nasal and/or sinus drainage

Warnings

Liver warning:

This product contains acetaminophen. Severe liver damage may occur if

- adult takes more than 4 doses (15 mL each) in 24 hrs, which is the maximum daily amount for this product
- taken with other drugs containing acetaminophen
- adult has 3 or more alcoholic drinks every day while using this product

Allergy Alert:

Acetaminophen may cause severe skin reactions.

Symptoms may include:

- skin reddening
- blisters
- rash

If a skin reaction occurs, stop use and seek medical help right away.

Sore throat warning:

If sore throat is severe, persists for more than 2 days, is accompanied or followed by fever, headache, rash, nausea, or vomiting, consult a doctor promptly.

Do not use

- with any other drug containing acetaminophen (prescription or nonprescription). If you are not sure whether a drug contains acetaminophen, ask a doctor or pharmacist.
- if you are now taking a prescription monoamine oxidase inhibitor (MAOI) (certain drugs for depression, psychiatric or emotional conditions, or Parkinson's disease), or for 2 weeks after stopping the MAOI drug. If you do not know if your prescription drug contains an MAOI, ask a doctor or pharmacist before taking this product.

Ask a doctor before use if you have

- liver disease
- heart disease
- high blood pressure
- thyroid disease
- diabetes
- glaucoma
- trouble urinating due to enlarged prostate gland
- cough that occurs with too much phlegm (mucus)
- persistent or chronic cough such as occurs with smoking, asthma, chronic bronchitis, or emphysema
- a sodium-restricted diet

Ask a doctor or pharmacist before use if you are

- taking the blood thinning drug warfarin.
- taking sedatives or tranquilizer

When using this product,

- do not use more than directed
- excitability may occur, especially in children
- marked drowsiness may occur
- avoid alcoholic drinks
- be careful when driving a motor vehicle or operating machinery
- alcohol, sedatives, and tranquilizers may increase drowsiness

Stop use and ask a doctor if

- you get nervous, dizzy or sleepless
- pain, nasal congestion, or cough gets worse or lasts more than 5 days (children) or 7 days (adults)
- fever gets worse or lasts more than 3 days
- redness or swelling is present
- new symptoms occur
- cough comes back or occurs with rash or headache that lasts.

These could be signs of a serious condition.

PREGNANCY OR BREAST FEEDING

If pregnant or breast-feeding,ask a health professional before use.

Keep out of reach of children.

In case of overdose, get medical help or contact a Poison Control Center right away. Quick medical attention is critical for adults as well as for children even if you do not notice any signs or symptoms.

Directions

- mL = milliliter
- take only as directed
- do not exceed 4 doses (4 Sachets) per 24 hours
- follow the instruction given on this carton for your easy use

Age (Years) | Dose (mL)
adults & children 12 yrs & over | 15 mL (1 Sachet) every 4 hours
children 4 to under 12 yrs | ask a doctor
children under 4 yrs | do not use

Other information

- store between 20-25°C (68-77°F)
- do not use if carton or sachet is torn, broken or punctured.

Inactive ingredients

citric acid anhydrous, FD&C Red No. 40, FD&C Blue No. 2, flavor, glycerin, propylene glycol, purified water, saccharin sodium, sodium benzoate, sodium citrate, sorbitol solution, sucralose, xanthan gum, stevia powder, menthol, sodium edetate.

QUESTIONS

Question or comments?

call 1-516-675-8915

RECENT MAJOR CHANGES

change